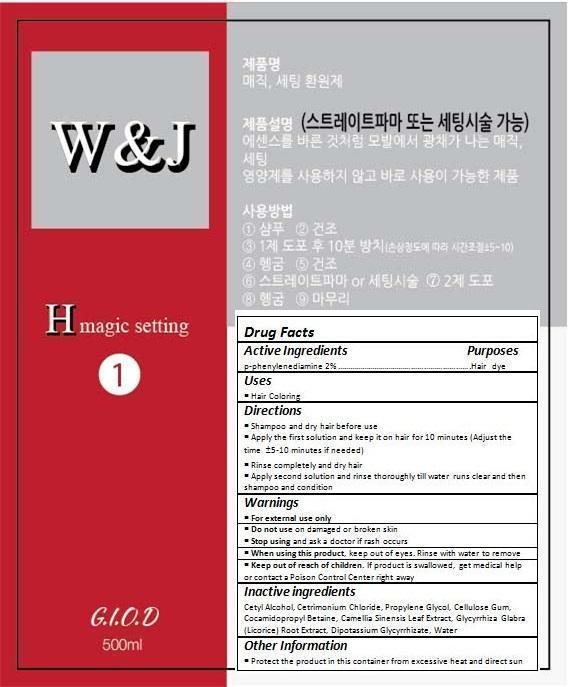 DRUG LABEL: ELF Color
NDC: 70072-002 | Form: CREAM
Manufacturer: giod Co.
Category: otc | Type: HUMAN OTC DRUG LABEL
Date: 20150905

ACTIVE INGREDIENTS: P-PHENYLENEDIAMINE 9.58 g/479.39 g
INACTIVE INGREDIENTS: CETYL ALCOHOL; CETRIMONIUM CHLORIDE; PROPYLENE GLYCOL; CARBOXYMETHYLCELLULOSE SODIUM, UNSPECIFIED FORM; COCAMIDOPROPYL BETAINE; GREEN TEA LEAF; GLYCYRRHIZA GLABRA; GLYCYRRHIZINATE DIPOTASSIUM; WATER

Drug Facts

ACTIVE INGREDIENT

p-phenylenediamine 2%

PURPOSE

Hair Coloring

INDICATIONS AND USAGE

Shampoo and dry hair before use
Apply the first solution and keep it on hair for 10 minutes (Adjust the time ±5-10 minutes if needed)
Rinse completely and dry hair
Apply second solution and rinse thoroughly till water runs clear and then shampoo and condition

DOSAGE AND ADMINISTRATION

Shampoo and dry hair before use
Apply the first solution and keep it on hair for 10 minutes (Adjust the time ±5-10 minutes if needed)
Rinse completely and dry hair
Apply second solution and rinse thoroughly till water runs clear and then shampoo and condition

WARNINGS

For external use only.
Do not use on damaged or broken skin.
When using this product, keep out of eyes. Rinse with water to remove.
Stop using and ask a doctor if rash occurs.

KEEP OUT OF REACH OF CHILDREN

Keep out of reach of the children. If product is swallowed, get medical help or contact a poison control center right away.

INACTIVE INGREDIENT

Cetyl Alcohol, Cetrimonium Chloride, Propylene Glycol, Cellulose Gum, Cocamidopropyl Betaine, Camellia Sinensis Leaf Extract, Glycyrrhiza Glabra (Licorice) Root Extract, Dipotassium Glycyrrhizate, Water